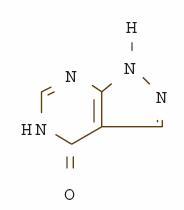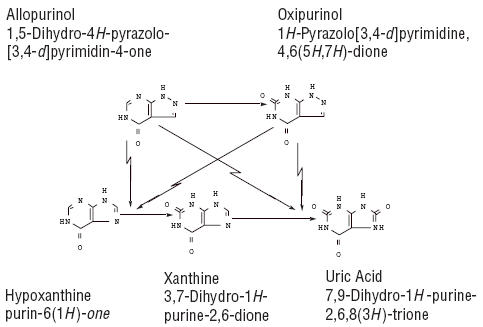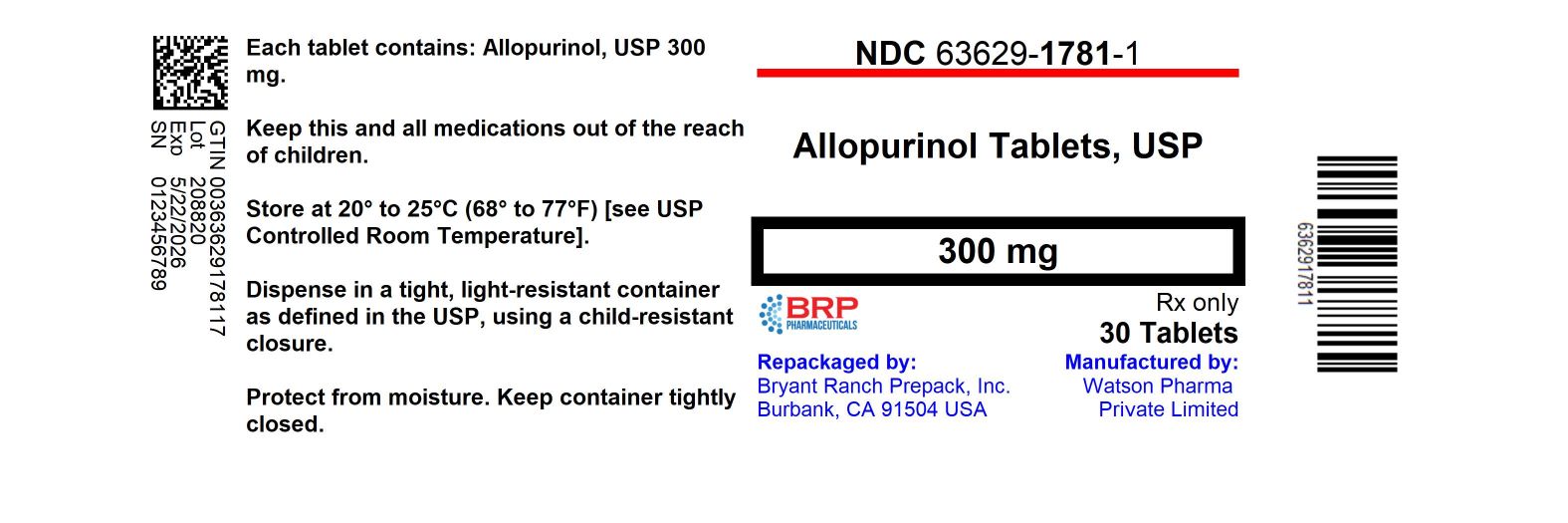 DRUG LABEL: Allopurinol
NDC: 63629-1781 | Form: TABLET
Manufacturer: Bryant Ranch Prepack
Category: prescription | Type: HUMAN PRESCRIPTION DRUG LABEL
Date: 20240522

ACTIVE INGREDIENTS: ALLOPURINOL 300 mg/1 1
INACTIVE INGREDIENTS: CROSCARMELLOSE SODIUM; LACTOSE MONOHYDRATE; MAGNESIUM STEARATE; MICROCRYSTALLINE CELLULOSE; STARCH, CORN; SODIUM LAURYL SULFATE; FD&C YELLOW NO. 6

Allopurinol
Tablets USP
Rx only

DESCRIPTION

Allopurinol, USP is known chemically as 1,5-dihydro-4H-pyrazolo [3,4-d ]pyrimidin-4-one. It is a xanthine oxidase inhibitor which is administered orally. Its solubility in water at 37°C is 80.0 mg/dL and is greater in an alkaline solution. The structural formula is represented below:

C5H4N4O M.W. 136.11

Allopurinol Tablets USP, 100 mg and 300 mg contain the following inactive ingredients: croscarmellose sodium, lactose monohydrate, magnesium stearate, microcrystalline cellulose, pregelatinized corn starch and sodium lauryl sulfate.

Allopurinol Tablets USP, 300 mg also contain FD&C Yellow No. 6.

CLINICAL PHARMACOLOGY

Allopurinol acts on purine catabolism, without disrupting the biosynthesis of purines. It reduces the production of uric acid by inhibiting the biochemical reactions immediately preceding its formation.

Allopurinol is a structural analogue of the natural purine base, hypoxanthine. It is an inhibitor of xanthine oxidase, the enzyme responsible for the conversion of hypoxanthine to xanthine and of xanthine to uric acid, the end product of purine metabolism in man. Allopurinol is metabolized to the corresponding xanthine analogue, oxipurinol (alloxanthine), which also is an inhibitor of xanthine oxidase.

It has been shown that reutilization of both hypoxanthine and xanthine for nucleotide and nucleic acid synthesis is markedly enhanced when their oxidations are inhibited by allopurinol and oxipurinol. This reutilization does not disrupt normal nucleic acid anabolism, however, because feedback inhibition is an integral part of purine biosynthesis. As a result of xanthine oxidase inhibition, the serum concentration of hypoxanthine plus xanthine in patients receiving allopurinol for treatment of hyperuricemia is usually in the range of 0.3 to 0.4 mg/dL compared to a normal level of approximately 0.15 mg/dL. A maximum of 0.9 mg/dL of these oxypurines has been reported when the serum urate was lowered to less than 2 mg/dL by high doses of allopurinol. These values are far below the saturation levels at which point their precipitation would be expected to occur (above 7 mg/dL).

The renal clearance of hypoxanthine and xanthine is at least 10 times greater than that of uric acid. The increased xanthine and hypoxanthine in the urine have not been accompanied by problems of nephrolithiasis. Xanthine crystalluria has been reported in only three patients. Two of the patients had Lesch-Nyhan syndrome, which is characterized by excessive uric acid production combined with a deficiency of the enzyme, hypoxanthine-guanine phosphoribosyltransferase (HGPRTase). This enzyme is required for the conversion of hypoxanthine, xanthine, and guanine to their respective nucleotides. The third patient had lymphosarcoma and produced an extremely large amount of uric acid because of rapid cell lysis during chemotherapy.

Allopurinol is approximately 90% absorbed from the gastrointestinal tract. Peak plasma levels generally occur at 1.5 hours and 4.5 hours for allopurinol and oxipurinol, respectively, and after a single oral dose of 300 mg allopurinol, maximum plasma levels of about 3 mcg/mL of allopurinol and 6.5 mcg/mL of oxipurinol are produced.

Approximately 20% of the ingested allopurinol is excreted in the feces. Because of its rapid oxidation to oxipurinol and a renal clearance rate approximately that of glomerular filtration rate, allopurinol has a plasma half-life of about 1 to 2 hours. Oxipurinol, however, has a longer plasma half-life (approximately 15 hours) and therefore effective xanthine oxidase inhibition is maintained over a 24-hour period with single daily doses of allopurinol. Whereas allopurinol is cleared essentially by glomerular filtration, oxipurinol is reabsorbed in the kidney tubules in a manner similar to the reabsorption of uric acid.

The clearance of oxipurinol is increased by uricosuric drugs, and as a consequence, the addition of a uricosuric agent reduces to some degree the inhibition of xanthine oxidase by oxipurinol and increases to some degree the urinary excretion of uric acid. In practice, the net effect of such combined therapy may be useful in some patients in achieving minimum serum uric acid levels provided the total urinary uric acid load does not exceed the competence of the patient’s renal function.

Hyperuricemia may be primary, as in gout, or secondary to diseases such as acute and chronic leukemia, polycythemia vera, multiple myeloma, and psoriasis. It may occur with the use of diuretic agents, during renal dialysis, in the presence of renal damage, during starvation or reducing diets, and in the treatment of neoplastic disease where rapid resolution of tissue masses may occur. Asymptomatic hyperuricemia is not an indication for treatment with allopurinol (see INDICATIONS AND USAGE).

Gout is a metabolic disorder which is characterized by hyperuricemia and resultant deposition of monosodium urate in the tissues, particularly the joints and kidneys. The etiology of this hyperuricemia is the overproduction of uric acid in relation to the patient’s ability to excrete it. If progressive deposition of urates is to be arrested or reversed, it is necessary to reduce the serum uric acid level below the saturation point to suppress urate precipitation.

Administration of allopurinol generally results in a fall in both serum and urinary uric acid within 2 to 3 days. The degree of this decrease can be manipulated almost at will since it is dose-dependent. A week or more of treatment with allopurinol may be required before its full effects are manifested; likewise, uric acid may return to pretreatment levels slowly (usually after a period of 7 to 10 days following cessation of therapy). This reflects primarily the accumulation and slow clearance of oxipurinol. In some patients a dramatic fall in urinary uric acid excretion may not occur, particularly in those with severe tophaceous gout. It has been postulated that this may be due to the mobilization of urate from tissue deposits as the serum uric acid level begins to fall.

The action of allopurinol differs from that of uricosuric agents, which lower the serum uric acid level by increasing urinary excretion of uric acid. Allopurinol reduces both the serum and urinary uric acid levels by inhibiting the formation of uric acid. The use of allopurinol to block the formation of urates avoids the hazard of increased renal excretion of uric acid posed by uricosuric drugs.

Allopurinol can substantially reduce serum and urinary uric acid levels in previously refractory patients even in the presence of renal damage serious enough to render uricosuric drugs virtually ineffective. Salicylates may be given conjointly for their antirheumatic effect without compromising the action of allopurinol. This is in contrast to the nullifying effect of salicylates on uricosuric drugs.

Allopurinol also inhibits the enzymatic oxidation of mercaptopurine, the sulfur-containing analogue of hypoxanthine, to 6-thiouric acid. This oxidation, which is catalyzed by xanthine oxidase, inactivates mercaptopurine. Hence, the inhibition of such oxidation by allopurinol may result in as much as a 75% reduction in the therapeutic dose requirement of mercaptopurine when the two compounds are given together.

INDICATIONS AND USAGE

THIS IS NOT AN INNOCUOUS DRUG. IT IS NOT RECOMMENDED FOR THE TREATMENT OF ASYMPTOMATIC HYPERURICEMIA.

Allopurinol reduces serum and urinary uric acid concentrations. Its use should be individualized for each patient and requires an understanding of its mode of action and pharmacokinetics (see CLINICAL PHARMACOLOGY, CONTRAINDICATIONS, WARNINGS, and PRECAUTIONS).

Allopurinol is indicated in:

1. the management of patients with signs and symptoms of primary or secondary gout (acute attacks, tophi, joint destruction, uric acid lithiasis, and/or nephropathy).
2. the management of patients with leukemia, lymphoma and malignancies who are receiving cancer therapy which causes elevations of serum and urinary uric acid levels. Treatment with allopurinol should be discontinued when the potential for overproduction of uric acid is no longer present.
3. the management of patients with recurrent calcium oxalate calculi whose daily uric acid excretion exceeds 800 mg/day in male patients and 750 mg/day in female patients. Therapy in such patients should be carefully assessed initially and reassessed periodically to determine in each case that treatment is beneficial and that the benefits outweigh the risks.

CONTRAINDICATIONS

Patients who have developed a severe reaction to allopurinol should not be restarted on the drug.

WARNINGS

ALLOPURINOL SHOULD BE DISCONTINUED AT THE FIRST APPEARANCE OF SKIN RASH OR OTHER SIGNS WHICH MAY INDICATE AN ALLERGIC REACTION. In some instances a skin rash may be followed by more severe hypersensitivity reactions such as exfoliative, urticarial, and purpuric lesions, as well as Stevens-Johnson syndrome (erythema multiforme exudativum), Drug Rash with Eosinophilia and Systemic Symptoms (DRESS) and/or generalized vasculitis, irreversible hepatotoxicity, and, on rare occasions, death (see ADVERSE REACTIONS).

In patients receiving mercaptopurine or azathioprine, the concomitant administration of 300 to 600 mg of allopurinol per day will require a reduction in dose to approximately one-third to one-fourth of the usual dose of mercaptopurine or azathioprine. Subsequent adjustment of doses of mercaptopurine or azathioprine should be made on the basis of therapeutic response and the appearance of toxic effects (see CLINICAL PHARMACOLOGY).

A few cases of reversible clinical hepatotoxicity have been noted in patients taking allopurinol, and in some patients, asymptomatic rises in serum alkaline phosphatase or serum transaminase have been observed. If anorexia, weight loss, or pruritus develop in patients on allopurinol, evaluation of liver function should be part of their diagnostic workup. In patients with pre-existing liver disease, periodic liver function tests are recommended during the early stages of therapy.

Due to the occasional occurrence of drowsiness, patients should be alerted to the need for due precaution when engaging in activities where alertness is mandatory.

The occurrence of hypersensitivity reactions to allopurinol may be increased in patients with decreased renal function receiving thiazides and allopurinol concurrently. For this reason, in this clinical setting, such combinations should be administered with caution and patients should be observed closely.

PRECAUTIONS

General

An increase in acute attacks of gout has been reported during the early stages of administration of allopurinol, even when normal or subnormal serum uric acid levels have been attained. Accordingly, maintenance doses of colchicine generally should be given prophylactically when allopurinol is begun. In addition, it is recommended that the patient start with a low dose of allopurinol (100 mg daily) and increase at weekly intervals by 100 mg until a serum uric acid level of 6 mg/dL or less is attained but without exceeding the maximum recommended dose (800 mg per day). The use of colchicine or anti-inflammatory agents may be required to suppress gouty attacks in some cases. The attacks usually become shorter and less severe after several months of therapy. The mobilization of urates from tissue deposits which cause fluctuations in the serum uric acid levels may be a possible explanation for these episodes. Even with adequate therapy with allopurinol, it may require several months to deplete the uric acid pool sufficiently to achieve control of the acute attacks.

A fluid intake sufficient to yield a daily urinary output of at least 2 liters and the maintenance of a neutral or, preferably, slightly alkaline urine are desirable to (1) avoid the theoretical possibility of formation of xanthine calculi under the influence of therapy with allopurinol and (2) help prevent renal precipitation of urates in patients receiving concomitant uricosuric agents.

Some patients with pre-existing renal disease or poor urate clearance have shown a rise in BUN during administration of allopurinol. Although the mechanism responsible for this has not been established, patients with impaired renal function should be carefully observed during the early stages of administration of allopurinol and the dosage decreased or the drug withdrawn if increased abnormalities in renal function appear and persist.

Renal failure in association with administration of allopurinol has been observed among patients with hyperuricemia secondary to neoplastic diseases. Concurrent conditions such as multiple myeloma and congestive myocardial disease were present among those patients whose renal dysfunction increased after allopurinol was begun. Renal failure is also frequently associated with gouty nephropathy and rarely with hypersensitivity reactions associated with allopurinol. Albuminuria has been observed among patients who developed clinical gout following chronic glomerulonephritis and chronic pyelonephritis.

Patients with decreased renal function require lower doses of allopurinol than those with normal renal function. Lower than recommended doses should be used to initiate therapy in any patients with decreased renal function and they should be observed closely during the early stages of administration of allopurinol. In patients with severely impaired renal function or decreased urate clearance, the half-life of oxipurinol in the plasma is greatly prolonged. Therefore, a dose of 100 mg per day or 300 mg twice a week, or perhaps less, may be sufficient to maintain adequate xanthine oxidase inhibition to reduce serum urate levels.

Bone marrow depression has been reported in patients receiving allopurinol, most of whom received concomitant drugs with the potential for causing this reaction. This has occurred as early as 6 weeks to as long as 6 years after the initiation of therapy of allopurinol. Rarely, a patient may develop varying degrees of bone marrow depression, affecting one or more cell lines, while receiving allopurinol alone.

Information for Patients

Patients should be informed of the following:
(1) They should be cautioned to discontinue allopurinol and to consult their physician immediately at the first sign of a skin rash, painful urination, blood in the urine, irritation of the eyes, or swelling of the lips or mouth. (2) They should be reminded to continue drug therapy prescribed for gouty attacks since optimal benefit of allopurinol may be delayed for 2 to 6 weeks. (3) They should be encouraged to increase fluid intake during therapy to prevent renal stones. (4) If a single dose of allopurinol is occasionally forgotten, there is no need to double the dose at the next scheduled time. (5) There may be certain risks associated with the concomitant use of allopurinol and dicumarol, sulfinpyrazone, mercaptopurine, azathioprine, ampicillin, amoxicillin, and thiazide diuretics, and they should follow the instructions of their physician. (6) Due to the occasional occurrence of drowsiness, patients should take precautions when engaging in activities where alertness is mandatory. (7) Patients may wish to take allopurinol after meals to minimize gastric irritation.

Laboratory Tests

The correct dosage and schedule for maintaining the serum uric acid within the normal range is best determined by using the serum uric acid as an index.

In patients with pre-existing liver disease, periodic liver function tests are recommended during the early stages of therapy (see WARNINGS).

Allopurinol and its primary active metabolite, oxipurinol, are eliminated by the kidneys; therefore, changes in renal function have a profound effect on dosage. In patients with decreased renal function or who have concurrent illnesses which can affect renal function such as hypertension and diabetes mellitus, periodic laboratory parameters of renal function, particularly BUN and serum creatinine or creatinine clearance, should be performed and the patient’s dosage of allopurinol reassessed.

The prothrombin time should be reassessed periodically in the patients receiving dicumarol who are given allopurinol.

Drug Interactions

In patients receiving mercaptopurine or azathioprine, the concomitant administration of 300 to 600 mg of allopurinol per day will require a reduction in dose to approximately one-third to one-fourth of the usual dose of mercaptopurine or azathioprine. Subsequent adjustment of doses of mercaptopurine or azathioprine should be made on the basis of therapeutic response and the appearance of toxic effects (see CLINICAL PHARMACOLOGY).

It has been reported that allopurinol prolongs the half-life of the anticoagulant, dicumarol. The clinical basis of this drug interaction has not been established but should be noted when allopurinol is given to patients already on dicumarol therapy.

Since the excretion of oxipurinol is similar to that of urate, uricosuric agents, which increase the excretion of urate, are also likely to increase the excretion of oxipurinol and thus lower the degree of inhibition of xanthine oxidase. The concomitant administration of uricosuric agents and allopurinol has been associated with a decrease in the excretion of oxypurines (hypoxanthine and xanthine) and an increase in urinary uric acid excretion compared with that observed with allopurinol alone. Although clinical evidence to date has not demonstrated renal precipitation of oxypurines in patients either on allopurinol alone or in combination with uricosuric agents, the possibility should be kept in mind.

The reports that the concomitant use of allopurinol and thiazide diuretics may contribute to the enhancement of allopurinol toxicity in some patients have been reviewed in an attempt to establish a cause-and-effect relationship and a mechanism of causation. Review of these case reports indicates that the patients were mainly receiving thiazide diuretics for hypertension and that tests to rule out decreased renal function secondary to hypertensive nephropathy were not often performed. In those patients in whom renal insufficiency was documented, however, the recommendation to lower the dose of allopurinol was not followed. Although a causal mechanism and a cause-and-effect relationship have not been established, current evidence suggests that renal function should be monitored in patients on thiazide diuretics and allopurinol even in the absence of renal failure, and dosage levels should be even more conservatively adjusted in those patients on such combined therapy if diminished renal function is detected.

An increase in the frequency of skin rash has been reported among patients receiving ampicillin or amoxicillin concurrently with allopurinol compared to patients who are not receiving both drugs. The cause of the reported association has not been established.

Enhanced bone marrow suppression by cyclophosphamide and other cytotoxic agents has been reported among patients with neoplastic disease, except leukemia, in the presence of allopurinol. However, in a well-controlled study of patients with lymphoma on combination therapy, allopurinol did not increase the marrow toxicity of patients treated with cyclophosphamide, doxorubicin, bleomycin, procarbazine, and/or mechlorethamine.

Tolbutamide’s conversion to inactive metabolites has been shown to be catalyzed by xanthine oxidase from rat liver. The clinical significance, if any, of these observations is unknown.

Chlorpropamide’s plasma half-life may be prolonged by allopurinol, since allopurinol and chlorpropamide may compete for excretion in the renal tubule. The risk of hypoglycemia secondary to this mechanism may be increased if allopurinol and chlorpropamide are given concomitantly in the presence of renal insufficiency.

Rare reports indicate that cyclosporine levels may be increased during concomitant treatment with allopurinol. Monitoring of cyclosporine levels and possible adjustment of cyclosporine dosage should be considered when these drugs are co-administered.

Drug/Laboratory Test Interactions

Allopurinol is not known to alter the accuracy of laboratory tests.

Pregnancy

Teratogenic Effects

Reproductive studies have been performed in rats and rabbits at doses up to twenty times the usual human dose (5 mg/kg per day), and it was concluded that there was no impaired fertility or harm to the fetus due to allopurinol. There is a published report of a study in pregnant mice given 50 or 100 mg/kg allopurinol intraperitoneally on gestation days 10 or 13. There were increased numbers of dead fetuses in dams given 100 mg/kg allopurinol but not in those given 50 mg/kg. There were increased numbers of external malformations in fetuses at both doses of allopurinol on gestation day 10 and increased numbers of skeletal malformations in fetuses at both doses on gestation day 13. It cannot be determined whether this represented a fetal effect or an effect secondary to maternal toxicity. There are, however, no adequate or well-controlled studies in pregnant women. Because animal reproduction studies are not always predictive of human response, this drug should be used during pregnancy only if clearly needed.

Experience with allopurinol during human pregnancy has been limited partly because women of reproductive age rarely require treatment with allopurinol. However, in 2011, a literature publication case report describes the outcome of a full term pregnancy in a 35 year-old woman who had recurrent kidney stones since age 18 who took allopurinol throughout the pregnancy. The child had multiple complex birth defects and died at 8 days of life. A second report in 2013 (Hoeltzenbein M et al (2013); PLoS ONE 8(6): e66637), provided data on 31 prospectively ascertained pregnancies involving mothers exposed to allopurinol for varying durations during the first trimester. The overall rate of major fetal malformations and spontaneous abortions was reported to be within the normal expected range; however, one child had severe malformations similar to those described in the cited earlier case report.

Nursing Mothers

Allopurinol and oxipurinol have been found in the milk of a mother who was receiving allopurinol. Since the effect of allopurinol on the nursing infant is unknown, caution should be exercised when allopurinol is administered to a nursing woman.

Pediatric Use

Allopurinol is rarely indicated for use in children with the exception of those with hyperuricemia secondary to malignancy or to certain rare inborn errors of purine metabolism (see INDICATIONS AND USAGE and DOSAGE AND ADMINISTRATION).

ADVERSE REACTIONS

Data upon which the following estimates of incidence of adverse reactions are made are derived from experiences reported in the literature, unpublished clinical trials and voluntary reports since marketing of allopurinol began. Past experience suggested that the most frequent event following the initiation of allopurinol treatment was an increase in acute attacks of gout (average 6% in early studies). An analysis of current usage suggests that the incidence of acute gouty attacks has diminished to less than 1%. The explanation for this decrease has not been determined but may be due in part to initiating therapy more gradually (see PRECAUTIONS and DOSAGE AND ADMINISTRATION).

The most frequent adverse reaction to allopurinol is skin rash. Skin reactions can be severe and sometimes fatal. Therefore, treatment with allopurinol should be discontinued immediately if a rash develops (see WARNINGS). Some patients with the most severe reaction also had fever, chills, arthralgias, cholestatic jaundice, eosinophilia and mild leukocytosis or leukopenia. Among 55 patients with gout treated with allopurinol for 3 to 34 months (average greater than 1 year) and followed prospectively, Rundles observed that 3% of patients developed a type of drug reaction which was predominantly a pruritic maculopapular skin eruption, sometimes scaly or exfoliative. However, with current usage, skin reactions have been observed less frequently than 1%. The explanation for this decrease is not obvious. The incidence of skin rash may be increased in the presence of renal insufficiency. The frequency of skin rash among patients receiving ampicillin or amoxicillin concurrently with allopurinol has been reported to be increased (see PRECAUTIONS).

Drug rash with eosinophilia and systemic symptoms (DRESS) syndrome or drug hypersensitivity syndrome (DHS) has been reported in association with allopurinol use. The syndrome includes many of the severe reactions described above, and is potentially life-threatening and fatal. The syndrome is often characterized by fever, severe and profuse skin rash, elevated leukocyte counts and in particular, elevated eosinophil counts, lymphadenopathy, and multi-organ pathologies. Systemic symptoms often included, but were not limited to, the hepatic and renal systems. Symptoms involving the cardiac, gastrointestinal, lymphatic, pulmonary, and ophthalmic systems were also reported as occurring as part of the syndrome. It has been reported that symptoms may develop in approximately 1 week from initiating allopurinol therapy, but longer latency periods have also been reported.

To report SUSPECTED ADVERSE REACTIONS, contact Actavis at 1-800-272-5525 or FDA at 1-800-FDA-1088 or http://www.fda.gov/ for voluntary reporting of adverse reactions.

Most Common Reactions* Probably Causally Related:

Gastrointestinal: Diarrhea, nausea, alkaline phosphatase increase, SGOT/SGPT increase.

Metabolic and Nutritional: Acute attacks of gout.

Skin and Appendages: Rash, maculopapular rash.

*Early clinical studies and incidence rates from early clinical experience with allopurinol suggested that these adverse reactions were found to occur at a rate of greater than 1%. The most frequent event observed was acute attacks of gout following the initiation of therapy. Analyses of current usage suggest that the incidence of these adverse reactions is now less than 1%. The explanation for this decrease has not been determined, but it may be due to following recommended usage (see ADVERSE REACTIONS introduction, INDICATIONS AND USAGE, PRECAUTIONS, and DOSAGE AND ADMINISTRATION).

Incidence Less Than 1% Probably Causally Related:

Body As a Whole: Ecchymosis, fever, headache.

Cardiovascular: Necrotizing angiitis, vasculitis.

Gastrointestinal: Hepatic necrosis, granulomatous hepatitis, hepatomegaly, hyperbilirubinemia, cholestatic jaundice, vomiting, intermittent abdominal pain, gastritis, dyspepsia.

Hemic and Lymphatic: Thrombocytopenia, eosinophilia, leukocytosis, leukopenia.

Musculoskeletal: Myopathy, arthralgias.

Nervous: Peripheral neuropathy, neuritis, paresthesia, somnolence.

Respiratory: Epistaxis.

Skin and Appendages: Erythema multiforme exudativum (Stevens-Johnson syndrome), toxic epidermal necrolysis (Lyell’s syndrome), hypersensitivity vasculitis, purpura, vesicular bullous dermatitis, exfoliative dermatitis, eczematoid dermatitis, pruritus, urticaria, alopecia, onycholysis, lichen planus.

Special Senses: Taste loss/perversion.

Urogenital: Renal failure, uremia (see PRECAUTIONS).

Incidence Less Than 1% Causal Relationship Unknown:

Body As a Whole: Malaise.

Cardiovascular: Pericarditis, peripheral vascular disease, thrombophlebitis, bradycardia, vasodilation.

Endocrine: Infertility (male), hypercalcemia, gynecomastia (male).

Gastrointestinal: Hemorrhagic pancreatitis, gastrointestinal bleeding, stomatitis, salivary gland swelling, hyperlipidemia, tongue edema, anorexia.

Hemic and Lymphatic: Aplastic anemia, agranulocytosis, eosinophilic fibrohistiocytic lesion of bone marrow, pancytopenia, prothrombin decrease, anemia, hemolytic anemia, reticulocytosis, lymphadenopathy, lymphocytosis.

Musculoskeletal: Myalgia.

Nervous: Optic neuritis, confusion, dizziness, vertigo, foot drop, decrease in libido, depression, amnesia, tinnitus, asthenia, insomnia.

Respiratory: Bronchospasm, asthma, pharyngitis, rhinitis.

Skin and Appendages: Furunculosis, facial edema, sweating, skin edema.

Special Senses: Cataracts, macular retinitis, iritis, conjunctivitis, amblyopia.

Urogenital: Nephritis, impotence, primary hematuria, albuminuria.

OVERDOSAGE

Massive overdosing or acute poisoning by allopurinol has not been reported.

In mice, the 50% lethal dose (LD50) is 160 mg/kg given intraperitoneally (IP) with deaths delayed up to 5 days and 700 mg/kg orally (PO) (approximately 140 times the usual human dose) with deaths delayed up to 3 days. In rats, the acute LD50 is 750 mg/kg IP and 6000 mg/kg PO (approximately 1200 times the human dose).

In the management of overdosage there is no specific antidote for allopurinol. There has been no clinical experience in the management of a patient who has taken massive amounts of allopurinol.

Both allopurinol and oxipurinol are dialyzable; however, the usefulness of hemodialysis or peritoneal dialysis in the management of an overdose of allopurinol is unknown.

DOSAGE AND ADMINISTRATION

The dosage of allopurinol to accomplish full control of gout and to lower serum uric acid to normal or near-normal levels varies with the severity of the disease. The average is 200 to 300 mg/day for patients with mild gout and 400 to 600 mg/day for those with moderately severe tophaceous gout. The appropriate dosage may be administered in divided doses or as a single equivalent dose with the 300 mg tablet. Dosage requirements in excess of 300 mg should be administered in divided doses. The minimal effective dosage is 100 to 200 mg daily and the maximal recommended dosage is 800 mg daily. To reduce the possibility of flare-up of acute gouty attacks, it is recommended that the patient start with a low dose of allopurinol (100 mg daily) and increase at weekly intervals by 100 mg until a serum uric acid level of 6 mg/dL or less is attained but without exceeding the maximal recommended dosage.

Normal serum urate levels are usually achieved in 1 to 3 weeks. The upper limit of normal is about 7 mg/dL for men and postmenopausal women and 6 mg/dL for premenopausal women. Too much reliance should not be placed on a single serum uric acid determination since, for technical reasons, estimation of uric acid may be difficult. By selecting the appropriate dosage and, in certain patients, using uricosuric agents concurrently, it is possible to reduce serum uric acid to normal or, if desired, to as low as 2 to 3 mg/dL and keep it there indefinitely.

While adjusting the dosage of allopurinol in patients who are being treated with colchicine and/or anti-inflammatory agents, it is wise to continue the latter therapy until serum uric acid has been normalized and there has been freedom from acute gouty attacks for several months.

In transferring a patient from a uricosuric agent to allopurinol, the dose of the uricosuric agent should be gradually reduced over a period of several weeks and the dose of allopurinol gradually increased to the required dose needed to maintain a normal serum uric acid level.

It should also be noted that allopurinol is generally better tolerated if taken following meals. A fluid intake sufficient to yield a daily urinary output of at least 2 liters and the maintenance of a neutral or preferably, slightly alkaline urine are desirable.

Since allopurinol and its metabolites are primarily eliminated only by the kidney, accumulation of the drug can occur in renal failure, and the dose of allopurinol should consequently be reduced. With a creatinine clearance of 10 to 20 mL/min, a daily dosage of 200 mg of allopurinol is suitable. When the creatinine clearance is less than 10 mL/min, the daily dosage should not exceed 100 mg. With extreme renal impairment (creatinine clearance less than 3 mL/min) the interval between doses may also need to be lengthened.

The correct size and frequency of dosage for maintaining the serum uric acid just within the normal range is best determined by using the serum uric acid level as an index.

For the prevention of uric acid nephropathy during the vigorous therapy of neoplastic disease, treatment with 600 to 800 mg daily for 2 or 3 days is advisable together with a high fluid intake. Otherwise similar considerations to the above recommendations for treating patients with gout govern the regulation of dosage for maintenance purposes in secondary hyperuricemia.

The dose of allopurinol recommended for management of recurrent calcium oxalate stones in hyperuricosuric patients is 200 to 300 mg/day in divided doses or as the single equivalent. This dose may be adjusted up or down depending upon the resultant control of the hyperuricosuria based upon subsequent 24 hour urinary urate determinations. Clinical experience suggests that patients with recurrent calcium oxalate stones may also benefit from dietary changes such as the reduction of animal protein, sodium, refined sugars, oxalate-rich foods, and excessive calcium intake, as well as an increase in oral fluids and dietary fiber.

Children, 6 to 10 years of age, with secondary hyperuricemia associated with malignancies may be given 300 mg allopurinol daily while those under 6 years are generally given 150 mg daily. The response is evaluated after approximately 48 hours of therapy and a dosage adjustment is made if necessary.

HOW SUPPLIED

Product: 63629-1781

NDC: 63629-1781-4 90 TABLET in a BOTTLE

NDC: 63629-1781-1 30 TABLET in a BOTTLE

NDC: 63629-1781-2 60 TABLET in a BOTTLE

NDC: 63629-1781-3 100 TABLET in a BOTTLE

NDC: 63629-1781-5 20 TABLET in a BOTTLE

Repackaged/Relabeled by:

Bryant Ranch Prepack, Inc.

Burbank, CA 91504